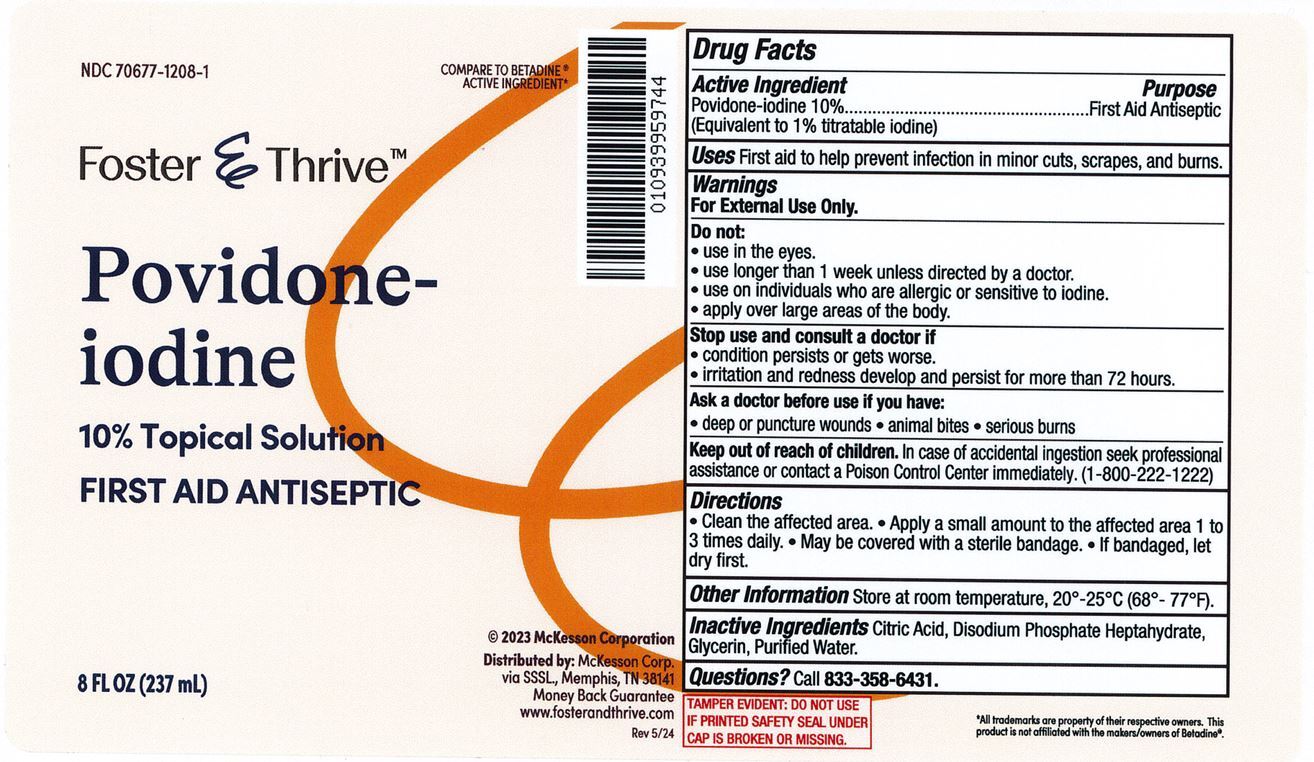 DRUG LABEL: Foster and Thrive Povidone-Iodine
NDC: 70677-1208 | Form: LIQUID
Manufacturer: Strategic Sourcing Services, LLC
Category: otc | Type: HUMAN OTC DRUG LABEL
Date: 20241203

ACTIVE INGREDIENTS: POVIDONE-IODINE 100 mg/1 mL
INACTIVE INGREDIENTS: CITRIC ACID MONOHYDRATE; SODIUM PHOSPHATE, DIBASIC; GLYCERIN; NONOXYNOL-9; WATER; SODIUM HYDROXIDE

Foster & Thrive Povidone-Iodine

Foster & Thrive Povidone-Iodine

Drug Facts

Active Ingredient

Povidone-Iodine 10% (1% Available iodine)

Purpose

First Aid Antiseptic

Uses

First aid to help prevent infection in in minor: cuts, scrapes and burns.

Warnings

For external use only

Do not use

in the eyes. Over large areas of the body.

Ask a doctor before use

in case of deep or puncture wounds, animal bites, or serious burns.

Stop use and consult a doctor if:

The condition persists or gets worse. Need to use this product for more than 1 week.

Keep out of reach of children.

- If swallowed, get medical help or contact a Poison Control Center right away.

Directions

- Clean the affected area. Apply a small amount to the affected area 1 to 3 times daily. May be covered with a sterile bandage. If bandaged, let dry first.

Inactive Ingredient

Citric acid, Dibasic sodium Phosphate, Glycerin, Nonoxynol-9, Purified water, sodium hydroxide.

Questions? Call 833-358-6431